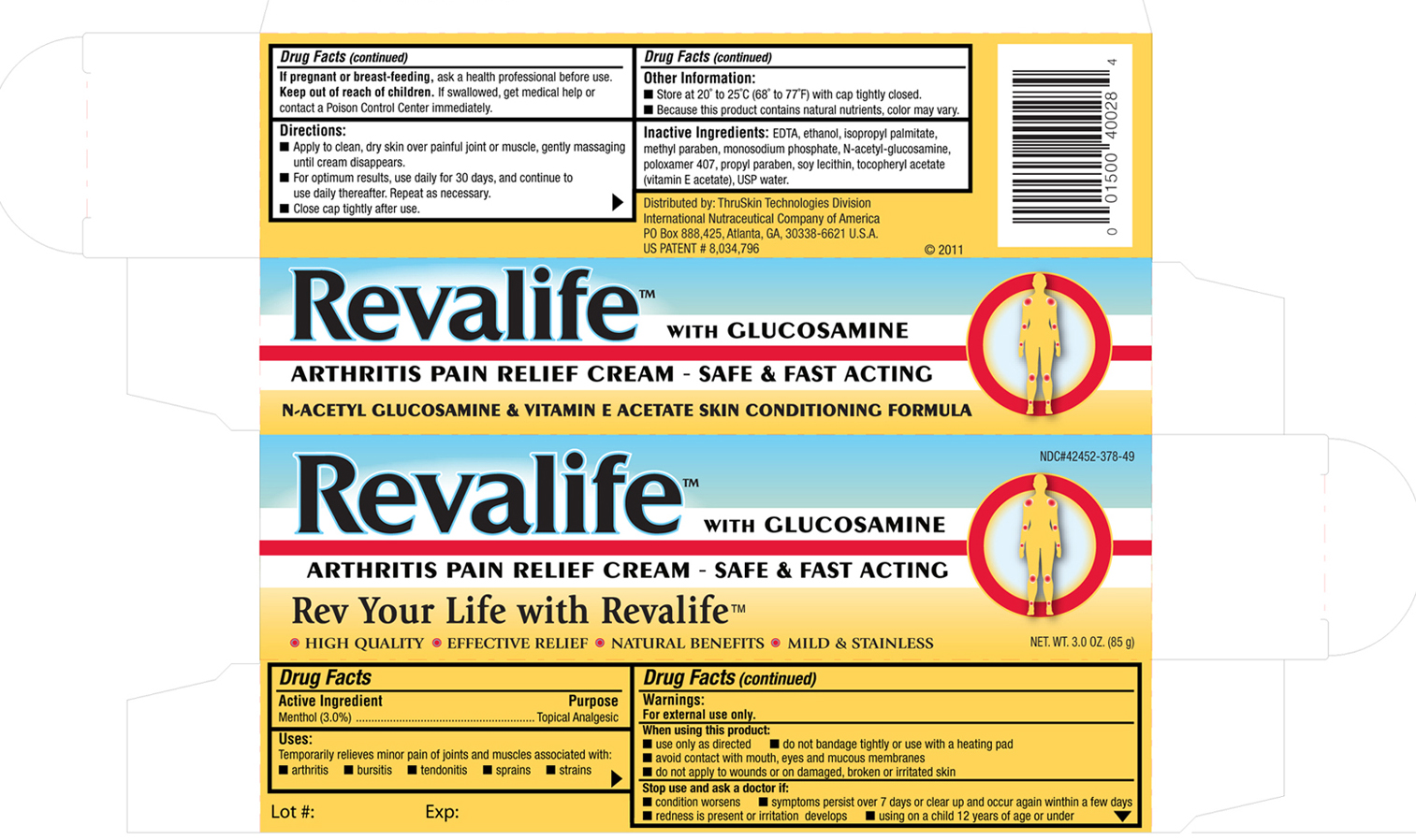 DRUG LABEL: Revalife
NDC: 42452-378 | Form: OINTMENT
Manufacturer: International Nutraceutical Company of America (INCA), LLC
Category: otc | Type: HUMAN OTC DRUG LABEL
Date: 20171206

ACTIVE INGREDIENTS: MENTHOL 937.5 mg/1 g
INACTIVE INGREDIENTS: ISOPROPYL PALMITATE; ALPHA-TOCOPHEROL; LECITHIN, SOYBEAN; ALCOHOL; METHYLPARABEN; PROPYLPARABEN; N-ACETYLGLUCOSAMINE

DRUG FACTS

Active Ingredient : Menthol 3%

Purpose-Topical Analgesic

INDICATIONS AND USAGE

Uses-Temporarily relieves minor pain of joints and muscles associated with arthritis, bursitis, tendonitis, strains

DOSAGE AND ADMINISTRATION

Directions: Apply to clean, dry skin over painful joint or muscle gently massaging until cream disappears. For optimum results use daily for 30 days and continue to use daily thereafter. Repeat as neccessary. Close cap tightly after use.

Keep out of reach of children. If swallowed, get medical help or contact a Poison Control Center right away.

WARNINGS

For external use only. Do not bandage tightly or use with a heating pad. Avoid contact with mouth, eyes, and mucous membranes. Do not apply to wounds, damaged, broken, or irritated skin.

Stop use and ask a doctor if: Symptoms persists over 7 day or clear up and occur again within a few days. Redness is present or irritation develops. Using on a child 12 years of age or under.

INACTIVE INGREDIENT

Inactive Ingredients: EDTA, Ethanol, Isopropyl palmitate, Methyl Paraben, Monosodium Phosphate, N-Acetyl Glucosamine, Poloxamer 407, Propyl Paraben, Soy Lecithin, Todopherol Acetate (Vitamin E), Water